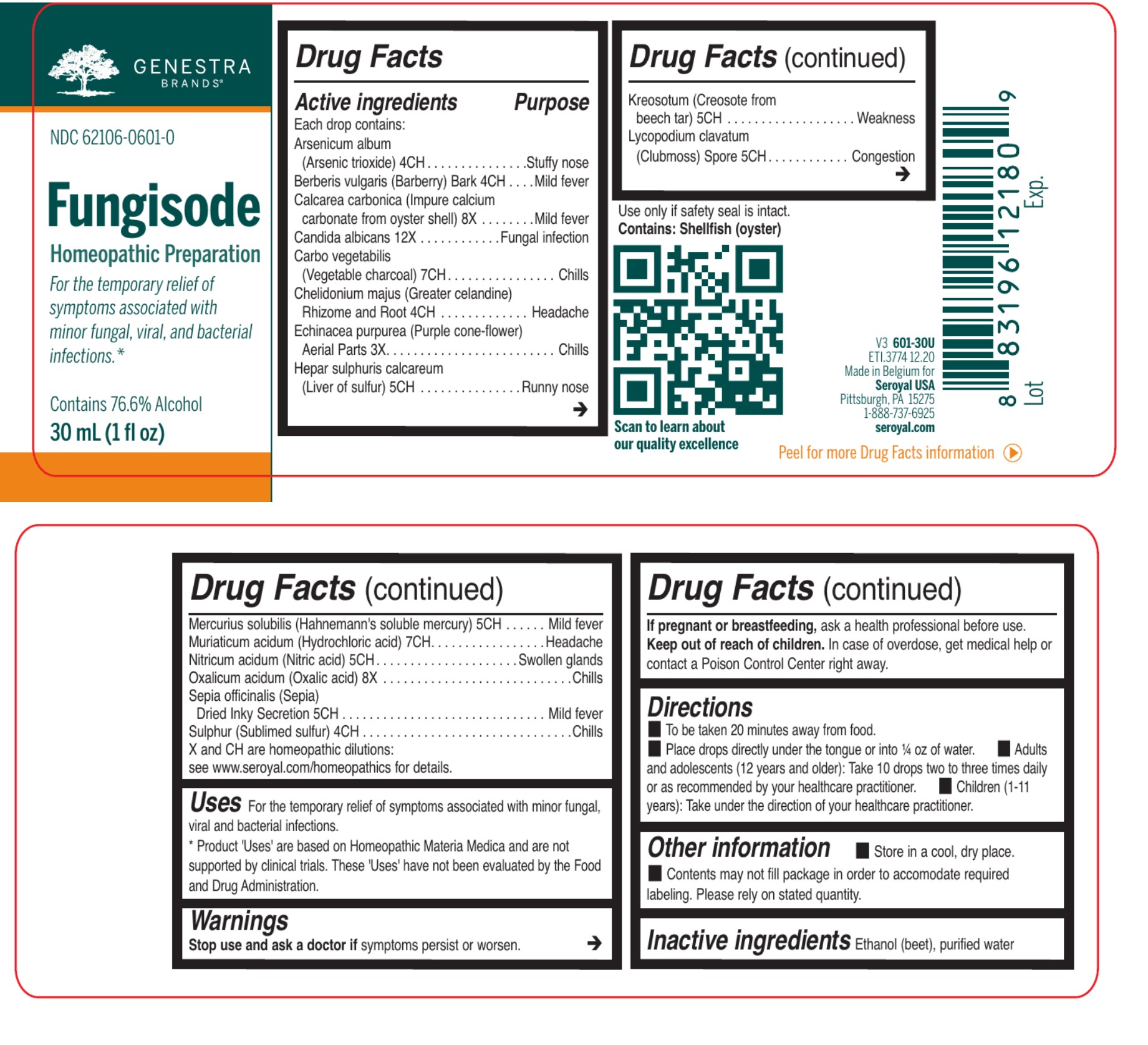 DRUG LABEL: Fungisode
NDC: 62106-0601 | Form: LIQUID
Manufacturer: Seroyal USA
Category: homeopathic | Type: HUMAN OTC DRUG LABEL
Date: 20210722

ACTIVE INGREDIENTS: ARSENIC TRIOXIDE 4 [hp_C]/30 mL; OYSTER SHELL CALCIUM CARBONATE, CRUDE 8 [hp_X]/30 mL; CANDIDA ALBICANS 12 [hp_X]/30 mL; ACTIVATED CHARCOAL 7 [hp_C]/30 mL; NITRIC ACID 5 [hp_C]/30 mL; WOOD CREOSOTE 5 [hp_C]/30 mL; MERCURIUS SOLUBILIS 5 [hp_C]/30 mL; BERBERIS VULGARIS ROOT BARK 4 [hp_C]/30 mL; ECHINACEA PURPUREA FLOWERING TOP 3 [hp_X]/30 mL; OXALIC ACID DIHYDRATE 8 [hp_X]/30 mL; SEPIA OFFICINALIS JUICE 5 [hp_C]/30 mL; SULFUR 4 [hp_C]/30 mL; CHELIDONIUM MAJUS ROOT 4 [hp_C]/30 mL; CALCIUM SULFIDE 5 [hp_C]/30 mL; LYCOPODIUM CLAVATUM SPORE 5 [hp_C]/30 mL; HYDROCHLORIC ACID 7 [hp_C]/30 mL
INACTIVE INGREDIENTS: WATER; ALCOHOL

Fungisode

Active ingredients
Each drop contains:
Arsenicum album (Arsenic trioxide) 4CH
Berberis vulgaris (Barberry) Bark 4CH
Calcarea carbonica (Impure calcium carbonate from oyster shell) 8X
Candida albicans 12X
Carbo vegetabilis (Vegetable charcoal) 7CH
Chelidonium majus (Greater celandine) Rhizome and Root 4CH
Echinacea purpurea (Purple cone-flower) Aerial Parts 3X
Hepar sulphuris calcareum (Liver of sulfur) 5CH
Kreosotum (Creosote from beech tar) 5CH

Lycopodium clavatum (Clubmoss) Spore 5CH

Mercurius solubilis (Hahnemann's soluble mercury) 5CH

Muriaticum acidum (Hydrochloric acid) 7CH
Nitricum acidum (Nitric acid) 5CH
Oxalicum acidum (Oxalic acid) 8X
Sepia officinalis (Sepia) Dried Inky Secretion 5CH
Sulphur (Sublimed sulfur) 4CH

Uses

For the temporary relief of symptoms associated with minor fungal, viral and bacterial infections.

Warnings
Stop use and ask a doctor if symptoms persist or worsen.

If pregnant or breastfeeding, ask a health professional before use.
Keep out of reach of children. In case of overdose, get medical help or contact a Poison Control Center right away.

Keep out of reach of children. In case of overdose, get medical help or contact a Poison Control Center right away.

PREGNANCY OR BREAST FEEDING

If pregnant or breastfeeding, ask a health professional before use.

Other information

Do not use if outer seal is missing or broken.

Store in a cool, dry place.

Inactive ingredients
Ethanol (beet), purified water

Directions

To be taken 20 minutes away from food.
Place drops directly under the tongue or into ¼ oz of water.

Adults and adolescents (12 years and older):

Take 10 drops two to three times daily or as recommended by your healthcare practitioner.

Children (under 12 years):

Take under the direction of your healthcare practitioner.

Uses

For the temporary relief of symptoms associated with minor fungal, viral and bacterial infections.

Directions

To be taken 20 minutes away from food.
Place drops directly under the tongue or into ¼ oz of water.

Adults and adolescents (12 years and older):

Take 10 drops two to three times daily or as recommended by your healthcare practitioner.

Children (under 12 years):

Take under the direction of your healthcare practitioner.

PACKAGE LABEL

NDC 62106-0601-0

Fungisode

HOMEOPATHIC PREPARATION

For the temporary relief of symptoms

associated with minor fungal, viral, and

bacterial infection.

Contains 76.6% Alcohol

1fl oz (30 mL)